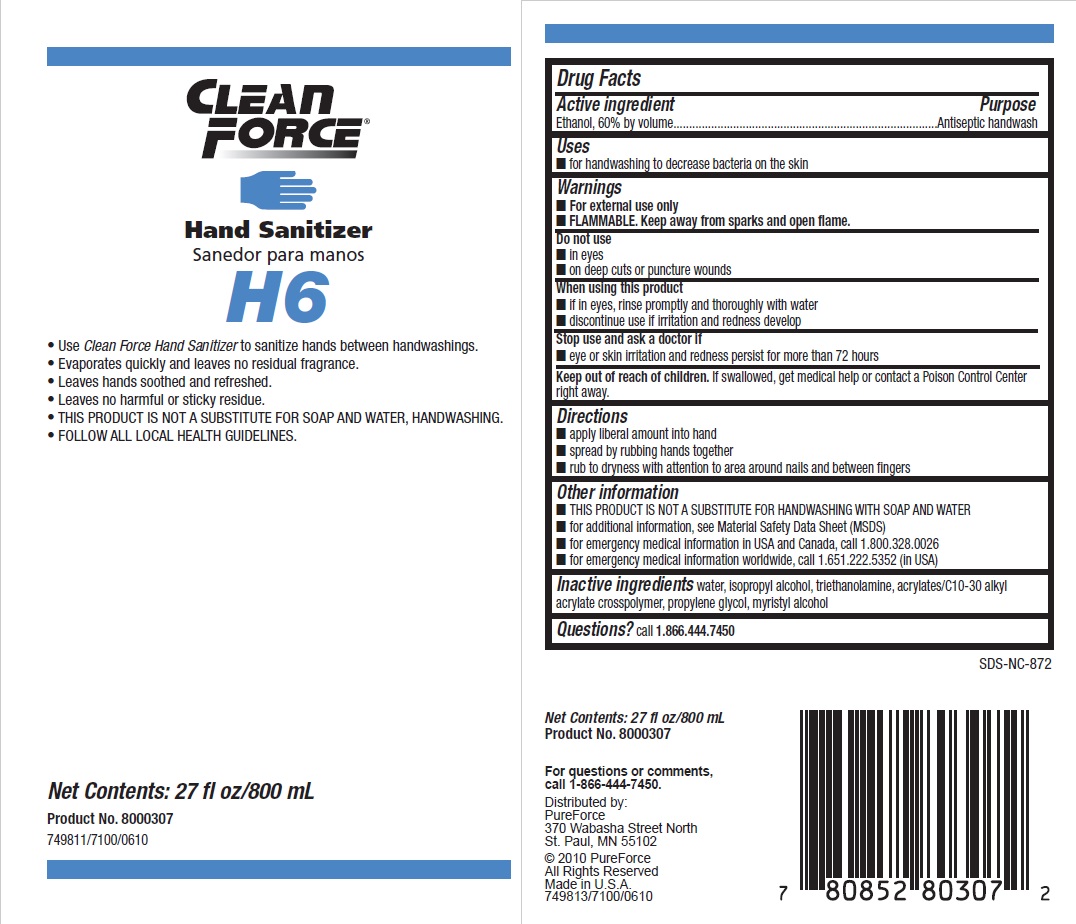 DRUG LABEL: Clean Force
NDC: 47593-406 | Form: SOLUTION
Manufacturer: Ecolab Inc.
Category: otc | Type: HUMAN OTC DRUG LABEL
Date: 20251210

ACTIVE INGREDIENTS: ALCOHOL 60 mL/100 mL
INACTIVE INGREDIENTS: CARBOMER COPOLYMER TYPE B (ALLYL PENTAERYTHRITOL CROSSLINKED); WATER; PROPYLENE GLYCOL; MYRISTYL ALCOHOL; ISOPROPYL ALCOHOL; TROLAMINE

Drug Facts

Active ingredient

Ethanol 60% by volume

Purpose

Antiseptic handwash

Uses

- for handwashing to decrease bacteria on the skin

Warnings

- For external use only
- Flammable, keep away from sparks and open flame

Do not use

- In eyes
- on deep cuts or puncture wounds

When using this product

- If in eyes, rinse promptly and thoroughly with water
- Discontinue use if irritation and redness develop

Stop use and ask a doctor if

- Eye or skin irritation and redness persist for more than 72 hours

Keep out of reach of children. If swallowed, get medical help or contact a Poison Control Center right away.

Directions

- Apply liberal amount into hand
- Spread by rubbing hands together
- Rub to dryness with attention to area around nails and between fingers

Other information

- THIS PRODUCT IS NOT A SUBSTITUTE FOR HANDWASHING WITH SOAP AND WATER
- for additional information, see Material Safety Data Sheet (MSDS)
- for emergency medical information in USA and Canada, call 1.800.328.0026
- for emergency medical information worldwide, call 1.651.222.5352 (in USA)

INACTIVE INGREDIENT

Inactive ingredients water, isopropyl alcohol, triethanolamine, acrylates/C10-30 alkyl acrylate crosspolymer, propylene glycol, myristyl alcohol

Questions? call 1.866.444.7450

Principal display panel and representative label

CLEAN FORCE

HAND SANITIZER

Use Clean Force Hand Sanitizer to sanitize hands between handwashings.

Evaporates quickly and leaves no residual fragrance.

Leaves hands soothed and refreshed.

Leaves no harmful or sticky residue.

THIS PRODUCT IS NOT A SUBSTITUTE FOR SOAP AND WATER, HANDWASHING.

FOLLOW ALL LOCAL HEALTH GUIDELINES.

Net Contents: 27 fl oz/800 mL

Product No. 8000307749811/7100/0610

Distributed by:

PureForce

370 Wabasha Street North

St. Paul, MN 55102

© 2010 PureForce

All Rights Reserved

Made in U.S.A.

749813/7100/0610